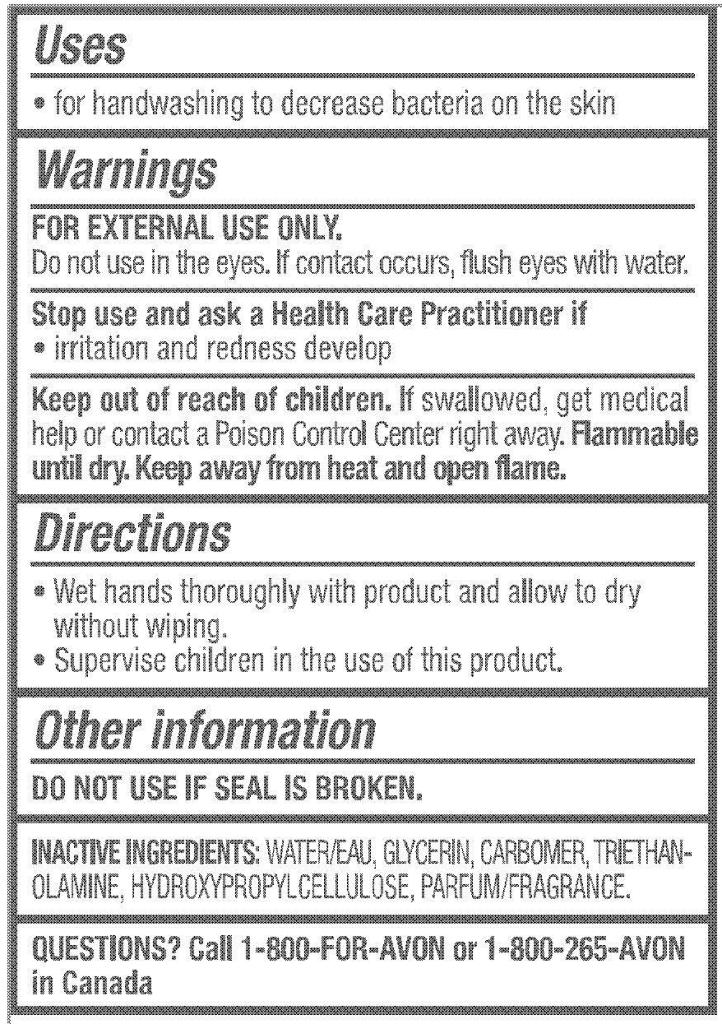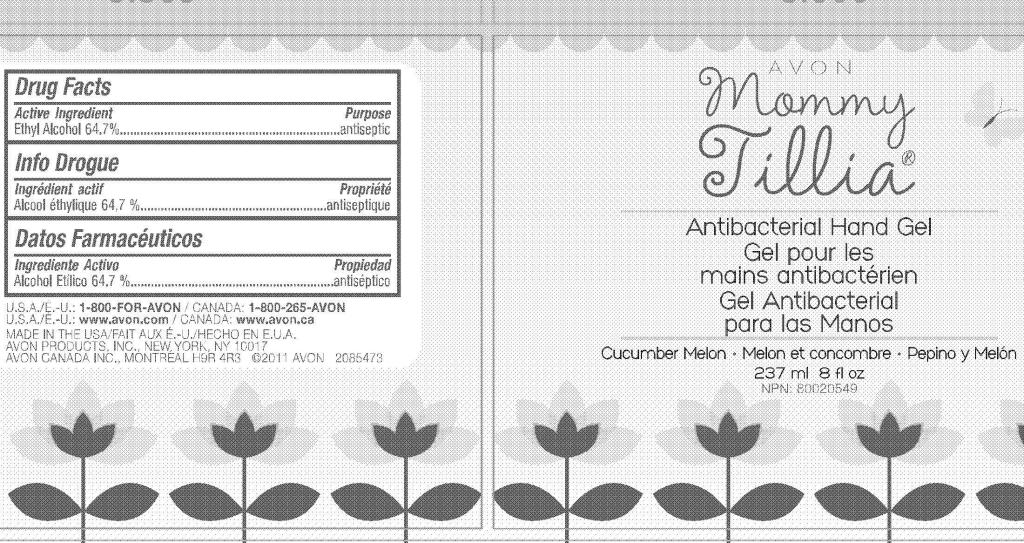 DRUG LABEL: Mommy Tillia
NDC: 10096-0238 | Form: GEL
Manufacturer: Avon Products, Inc.
Category: otc | Type: HUMAN OTC DRUG LABEL
Date: 20101220

ACTIVE INGREDIENTS: ALCOHOL	 153.34 mL/237 mL
INACTIVE INGREDIENTS: WATER	; GLYCERIN	

Drug Facts

Active Ingredient

Ethyl Alcohol 64.7%.......................

Purpose

...............antiseptic

Uses

- for handwashing to decrease bacteria on the skin

Warnings
FOR EXTERNAL USE ONLY.
Do not use in the eyes. If contact occurs, flush eyes with water.

Stop use and ask a Health Care Practitioner if

- irritation and redness develop

Keep out of reach of children. If swallowed, get medical help or contact a Poison Control Center right away. Flammable until dry. Keep away from heat and open flame.

Other information
DO NOT USE IF SEAL IS BROKEN.

INACTIVE INGREDIENTS: WATER/EAU
GLYCERIN
CARBOMER
TRIETHANOLAMINE
HYDROXYPROPYLCELLULOSE
PARFUM/FRAGRANCE

QUESTIONS

Questions? Call 1-800-FOR-AVON or 1-800-265-AVON in Canada

Directions

- Wet hands thoroughly with product and allow to dry without wiping.
- Supervise children in the use of this product.